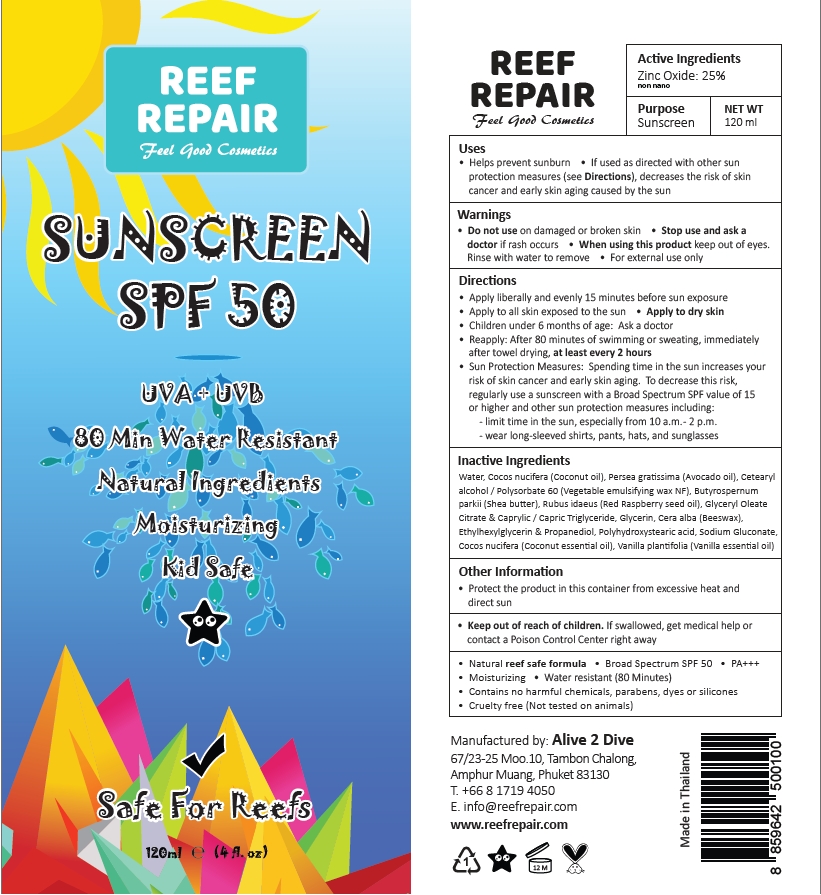 DRUG LABEL: Reef Repair SPF 50
NDC: 73541-000 | Form: CREAM
Manufacturer: Alive 2 Dive Company Limited
Category: otc | Type: HUMAN OTC DRUG LABEL
Date: 20240407

ACTIVE INGREDIENTS: ZINC OXIDE 25 g/100 mL
INACTIVE INGREDIENTS: SHEA BUTTER; GLYCERIN; WHITE WAX; ETHYLHEXYLGLYCERIN; VANILLA PLANIFOLIA OIL; COCOS NUCIFERA WHOLE; POLYHYDROXYSTEARIC ACID STEARATE; SODIUM GLUCONATE; TRICAPRIN; POLYSORBATE 60; PROPANEDIOL; AVOCADO OIL; RASPBERRY SEED OIL; GLYCERYL OLEATE

Reef Repair Suncream SPF 50+

Active ingredients

Zinc Oxide: 25%

Purpose

Sunscreen

Uses

- Helps prevent sunburn
- If used as directed with other sun protection measures (see Directions), decrease the risk of skin cancer and early skin aging caused by the sun

Directions

- Apply liberally and evenly to dry skin 15 minutes before sun exposure
- Apply to all skin exposed to the sun
- Reapply: After 80 minutes of swimming or sweating, immediately after towel drying, at least every 2 hours
- Sun Proctection Measures: Spending time in the sun increases your risk of skin cance and early skin aging. To decrease this risk, regularly use a sunscreen with a Broas Spectrum SPF calue of 15 or higher and other sun protection measures including:
- -limit time in the sun, especially from 10 a.m.-2 p.m.
- -wear long-sleeved shirts, pants, hats, and sunglasses

Warnings

- For external use only

Do not use on damaged or broken skin

Stop use and ask a doctor if rash occurs

When using this product keep out of eyes. Rinse with water to remove

Keep out of reach of children

If swallowed, get medical help or contact a Poison Control Center right away

Inactive Ingredients

Aqua, Cocos nuciera (Coconut oil), Persea gratissma (Avocado oil), Cetearyl alcohol / Polysorbate 60 (Vegatable emulsifying wax NF), Butyrospernum parkii (Shea butter), Rubus idaeus (Red Raspberry seed oil), Glyceryl Oleate Citrate & Caprylic / Capric Triglyceride, Glycerin, Cera alba (Beeswax), Ethylhexylglycerin & Propanediol, Polyhydoxystearic acid, Sodium Gluconate, Cocos nucifera (Coconut essential oil), Vanilla plantifolia (Vanilla essential oil)

Other Information

- 100 % biodegradable non-toxic, reef safe formula
- Contains no harmful chemicals, parabens or silicones
- Broad Spectrum SPF 50
- PA+++
- Moisturizing
- Cruelty free (Non tested on animals)
- Water resistant (80 Minutes)